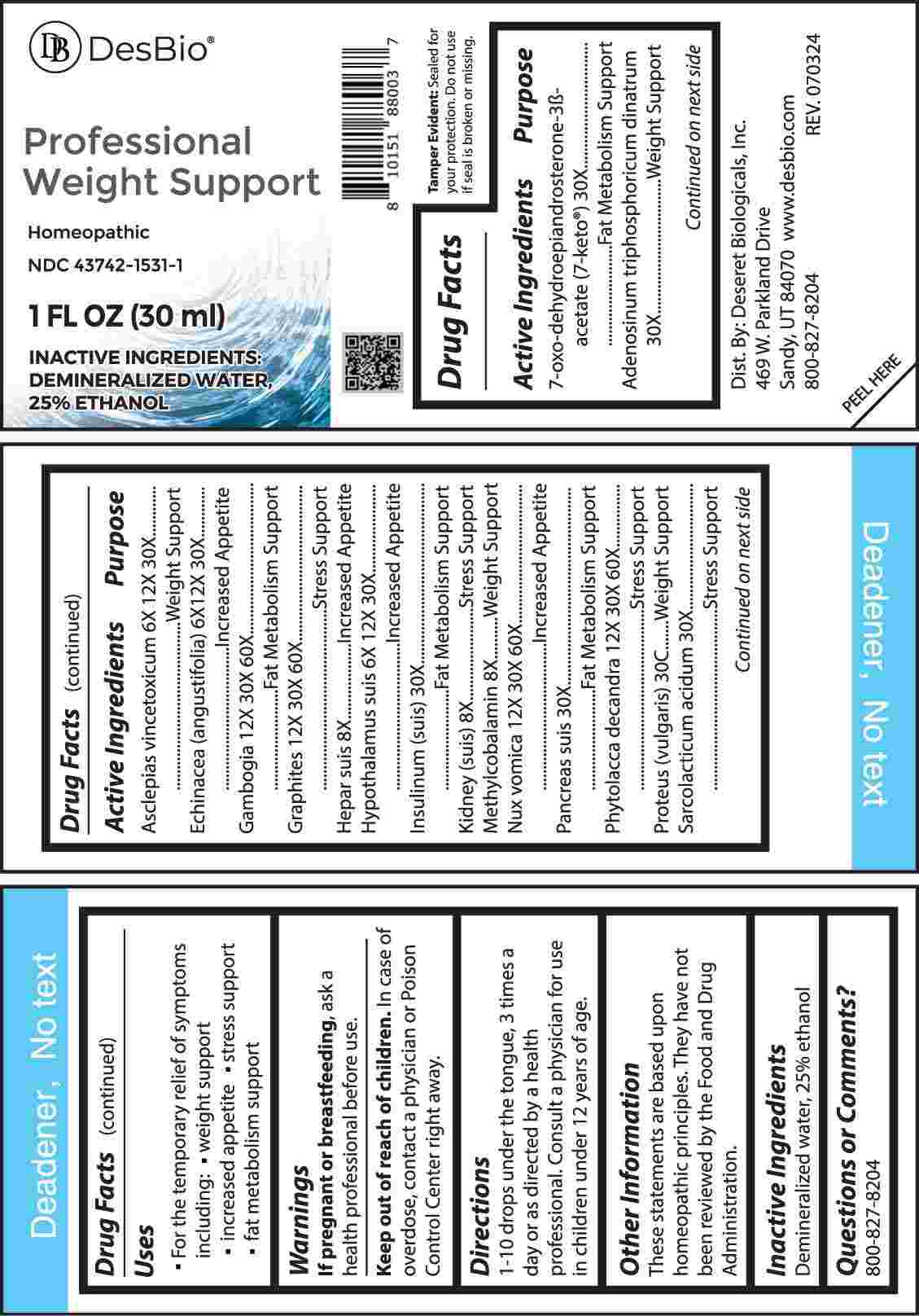 DRUG LABEL: Professional Weight Support
NDC: 43742-1531 | Form: LIQUID
Manufacturer: Deseret Biologicals, Inc.
Category: homeopathic | Type: HUMAN OTC DRUG LABEL
Date: 20241023

ACTIVE INGREDIENTS: CYNANCHUM VINCETOXICUM ROOT 6 [hp_X]/1 mL; ECHINACEA ANGUSTIFOLIA WHOLE 6 [hp_X]/1 mL; SUS SCROFA HYPOTHALAMUS 6 [hp_X]/1 mL; PORK LIVER 8 [hp_X]/1 mL; PORK KIDNEY 8 [hp_X]/1 mL; METHYLCOBALAMIN 8 [hp_X]/1 mL; GAMBOGE 12 [hp_X]/1 mL; GRAPHITE 12 [hp_X]/1 mL; STRYCHNOS NUX-VOMICA SEED 12 [hp_X]/1 mL; PHYTOLACCA AMERICANA ROOT 12 [hp_X]/1 mL; 7-OXODEHYDROEPIANDROSTERONE 3-ACETATE 30 [hp_X]/1 mL; ADENOSINE TRIPHOSPHATE DISODIUM 30 [hp_X]/1 mL; INSULIN PORK 30 [hp_X]/1 mL; SUS SCROFA PANCREAS 30 [hp_X]/1 mL; LACTIC ACID, L- 30 [hp_X]/1 mL; PROTEUS VULGARIS 30 [hp_C]/1 mL
INACTIVE INGREDIENTS: WATER; ALCOHOL

DRUG FACTS:

ACTIVE INGREDIENTS:

7-Oxo-Dehydroepiandrosterone 3-Acetate 30X, Adenosinum Triphosphoricum Dinatrum 30X, Asclepias Vincetoxicum 6X, 12X, 30X, Echinacea (Angustifolia) 6X, 12X, 30X, Gambogia 12X, 30X, 60X, Graphites 12X, 30X, 60X, Hepar Suis 8X, Hypothalamus Suis 6X, 12X, 30X, Insulinum (Suis) 30X, Kidney (Suis) 8X, Methylcobalamin 8X, Nux Vomica 12X, 30X, 60X, Pancreas Suis 30X, Phytolacca Decandra 12X, 30X, 60X, Proteus (Vulgaris) 30C, Sarcolacticum Acidum 30X.

PURPOSE:

7-Oxo-Dehydroepiandrosterone 3-Acetate – Fat Metabolism Support, Adenosinum Triphosphoricum Dinatrum – Weight Support, Asclepias Vincetoxicum – Weight Support, Echinacea (Angustifolia) – Increased Appetite, Gambogia – Fat Metabolism Support, Graphites – Stress Support, Hepar Suis – Increased Appetite, Hypothalamus Suis – Increased Appetite, Insulinum (Suis) – Fat Metabolism Support, Kidney (Suis) – Stress Support, Methylcobalamin – Weight Support, Nux Vomica – Increased Appetite, Pancreas Suis – Fat Metabolism Support, Phytolacca Decandra – Stress Support, Proteus (Vulgaris) – Weight Support, Sarcolacticum Acidum – Stress Support

USES:

• For the temporary relief of symptoms including:

• weight support • increased appetite • stress support • fat metabolism support

These statements are based upon homeopathic principles. They have not been reviewed by the Food and Drug Administration.

WARNINGS:

If pregnant or breast-feeding, ask a health professional before use.

Keep out of reach of children. In case of overdose, contact a physician or Poison Control Center right away.

Tamper Evident: Sealed for your protection. Do not use if seal is broken or missing.

KEEP OUT OF REACH OF CHILDREN:

In case of overdose, contact a physician or Poison Control Center right away.

DIRECTIONS:

1-10 drops under the tongue, 3 times a day or as directed by a health professional. Consult a physician for use in children under 12 years of age.

INACTIVE INGREDIENTS:

Demineralized water, 25% ethanol

QUESTIONS:

Dist. By: Deseret Biologicals, Inc.

469 W. Parkland Drive

Sandy, UT 84070

www.desbio.com

800-827-8204

PACKAGE LABEL DISPLAY:

Des Bio

Professional

Weight Support

Homeopathic

NDC 43742-1531-1

1 FL OZ (30 ml)